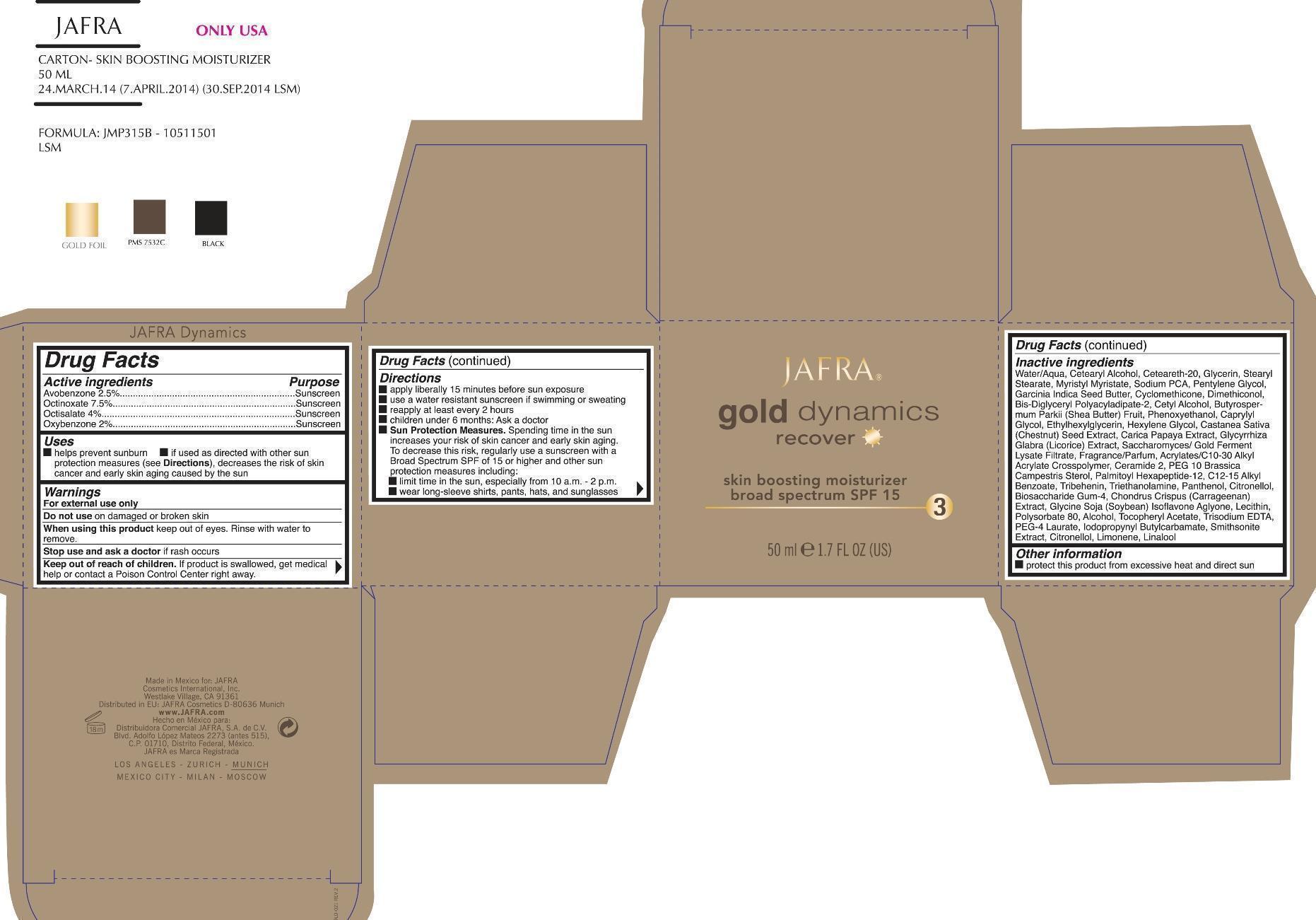 DRUG LABEL: recover skin boosting moisturizer broad spectrum SPF 15
NDC: 68828-202 | Form: CREAM
Manufacturer: Jafra Cosmetics International
Category: otc | Type: HUMAN OTC DRUG LABEL
Date: 20190607

ACTIVE INGREDIENTS: AVOBENZONE 2.5 g/100 mL; OCTINOXATE 7.5 g/100 mL; OCTISALATE 4 g/100 mL; OXYBENZONE 2 g/100 mL
INACTIVE INGREDIENTS: WATER; CETOSTEARYL ALCOHOL; POLYOXYL 20 CETOSTEARYL ETHER; GLYCERIN; STEARYL STEARATE; MYRISTYL MYRISTATE; SODIUM PYRROLIDONE CARBOXYLATE; PENTYLENE GLYCOL; GARCINIA INDICA SEED BUTTER; CYCLOMETHICONE; DIMETHICONOL (40 CST); CETYL ALCOHOL; SHEA BUTTER; PHENOXYETHANOL; CAPRYLYL GLYCOL; ETHYLHEXYLGLYCERIN; HEXYLENE GLYCOL; SPANISH CHESTNUT; PAPAYA; GLYCYRRHIZA GLABRA; CERAMIDE 2; ALKYL (C12-15) BENZOATE; TRIBEHENIN; TROLAMINE; PANTHENOL; .BETA.-CITRONELLOL, (R)-; BIOSACCHARIDE GUM-4; CHONDRUS CRISPUS CARRAGEENAN; EGG PHOSPHOLIPIDS; POLYSORBATE 80; ALCOHOL; .ALPHA.-TOCOPHEROL ACETATE; EDETATE TRISODIUM; PEG-4 LAURATE; IODOPROPYNYL BUTYLCARBAMATE; LIMONENE, (+/-)-; LINALOOL, (+/-)-

Gold Dynamics recover skin boosting moisturizer broad spectrum SPF 15

Active Ingredients Purpose

Avobenzone 2.5% Sunscreen

Octinoxate 7.5% Sunscreen

Octisalate 4% Sunscreen

Oxybenzone 2% Suncreen

Uses

- helps prevent sunburn
- if used as directed with other sun protection measure (see Directions), decreases the risk of skin cancer and early skin aging caused by the sun

Keep out of reach of children. if product is swallowed, get medical help or contact a Poison Contro Center right away.

Stop use and ask a doctor if rash occurs

Warnings

- For external use only
- Do not use on damaged or broken skin
- Wehn using this product keep out of eyes. Rinse with water to remove.

Directions

- apply liberally 15 minutes before sun exposure
- use a water resistant sunscrren if swimmng or sweating
- reapply at least every 2 hours
- children under 6 months: Ask a doctor
- Sun Protection Measures. Spending time in the sun increases your risk of skin cancer and early skin aging. To decrease this risk, regularly use a sunscreen with a Broad Spectrum SPF 15 or higher and other sun protection measures including:

limit time in the sun, especially from 10 a.m. - 2 p.m.

wear long-sleeve shirts, pants, hats, and sunglasses

Inactive ingredients

Water/Aqua, Cetearyl Alcohol, Ceteareth-20, Glycerin, Stearyl Stearate, Myristyl Myristate, Sodium PCA, Pentylene Glycol, Garcinia Indica Seed Butter, Cyclomethicone, Dimethiconol, Bis-Diglyceryl Polyacyladipate-2, Cetyl Alcohol, Butyrospermum Parkii (Shea Butter) Fruit, Phenoxyethanol, Caprylyl Glycol, Ethylhexylglycerin, Hexylene Glycol, Castanea Sativa (Chestnut) Seed Extract, Carica Papaya Extract, Glycyrrhiza Glabra (Licorice) Extract, Saccharomyces/ Gold Ferment Lysate Filtrate, Fragrance/Parfum, Acrylates/C10-30 Alkyl Acrylate Crosspolymer, Ceramide 2, PEG 10 Brassica Campestris Sterol, Palmitoyl Hexapeptide-12, C12-15 Alkyl Benzoate, Tribehenin, Triethanolamine, Panthenol, Citronellol, Biosaccharide Gum-4, Chondrus Crispus (Carrageenan) Extract, Glycine Soja (Soybean) Isoflavone Aglyone, Lecithin, Polysorbate 80, Alcohol, Tocopheryl Acetate, Trisodium EDTA, PEG-4 Laurate, Iodopropynyl Butylcarbamate, Smithsonite Extract, Citonellol, Limonene, Linalool

PACKAGE LABEL

Jafra

Gold dynamics recover

Skin boosting moisturizer broad spectrum SPF 15

50 ml 1.7 FL OZ.